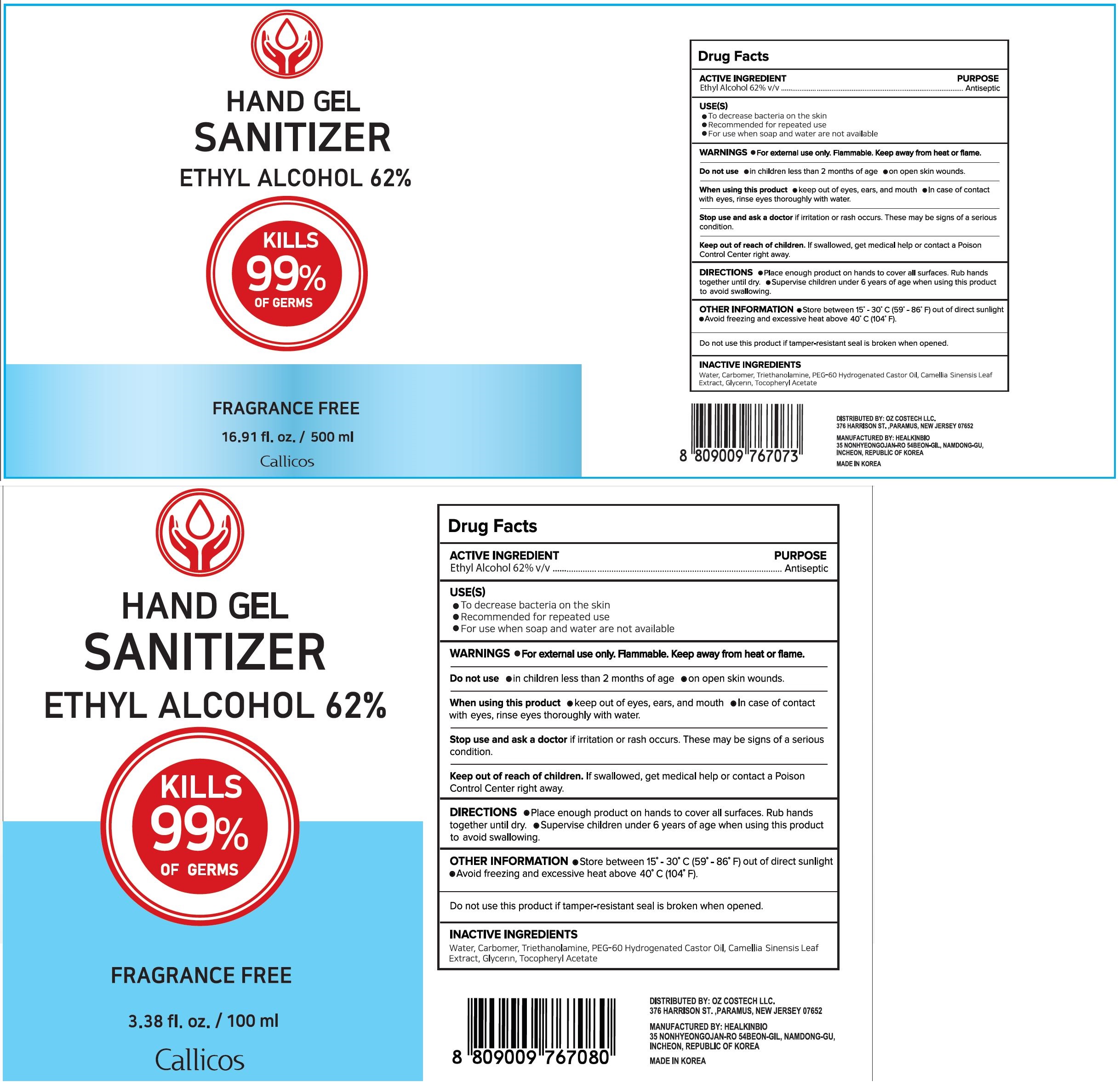 DRUG LABEL: Callicos Hand Gel Sanitizer
NDC: 76586-112 | Form: GEL
Manufacturer: HEALKINBIO CO.
Category: otc | Type: HUMAN OTC DRUG LABEL
Date: 20200830

ACTIVE INGREDIENTS: ALCOHOL 62 mL/100 mL
INACTIVE INGREDIENTS: TROLAMINE; .ALPHA.-TOCOPHEROL ACETATE; CARBOMER 940; GLYCERIN; PEG-60 HYDROGENATED CASTOR OIL; GREEN TEA LEAF

ACTIVE INGREDIENT

ethyl alcohol 62% v/v

Purpose

Antiseptic

Use

to decrease bacteria on the skin

recommended for repeated use

for use when soap and water are not available

Warnings

For external use only.
Flammable, keep away from fire or flame.

 Keep out of reach of children. If swallowed, get medical help or contact a Poison Control Center immediately.

Directions

place enough product on hands to cover all surfaces

rub hands together until dry

supervise children under 6 years of age when using this product to avoid swallowing

INACTIVE INGREDIENT

water, carbomer, triethaqnolamine, peg-60 hydrogenated castor oil, camellia sinensis leaf extract, glycerin, tocopheryl acetate

When using this product, avoid contact with the eyes. In case of contact, rinse eyes thoroughly with water.
Stop use and ask a doctor if irritation or redness appears and lasts.